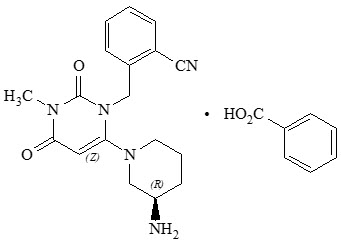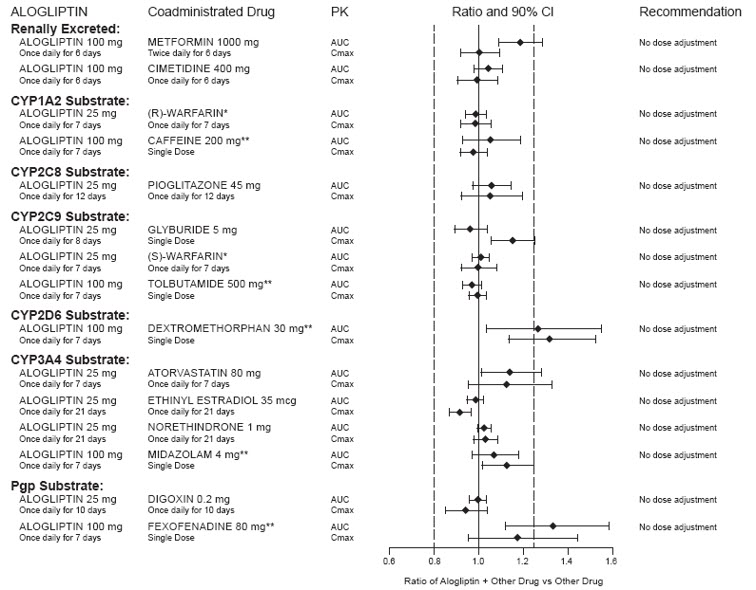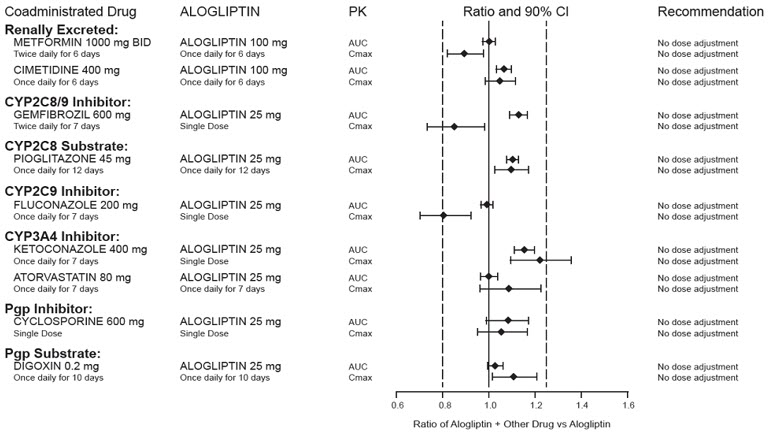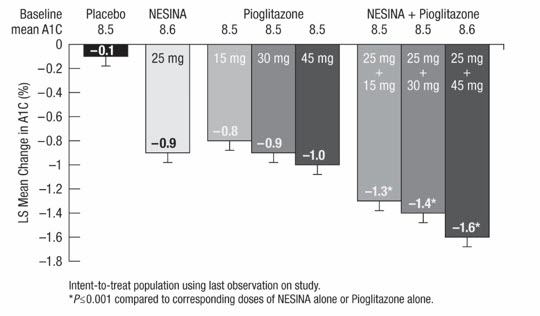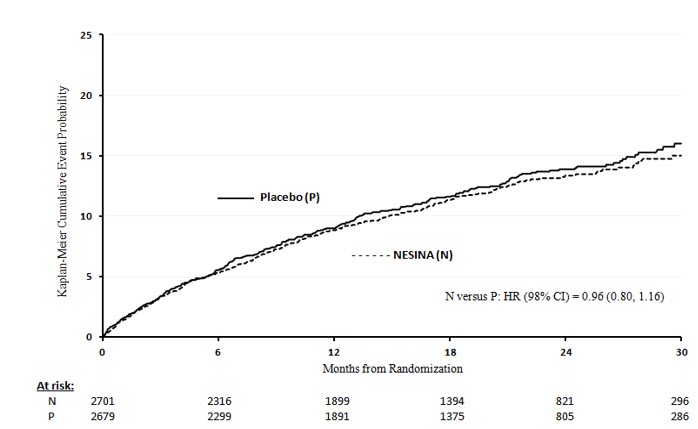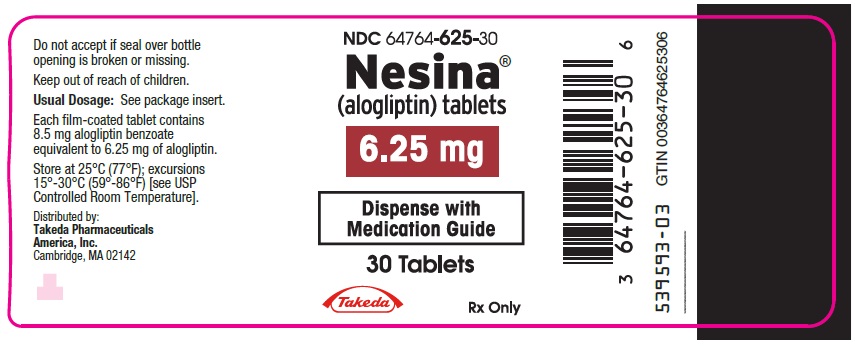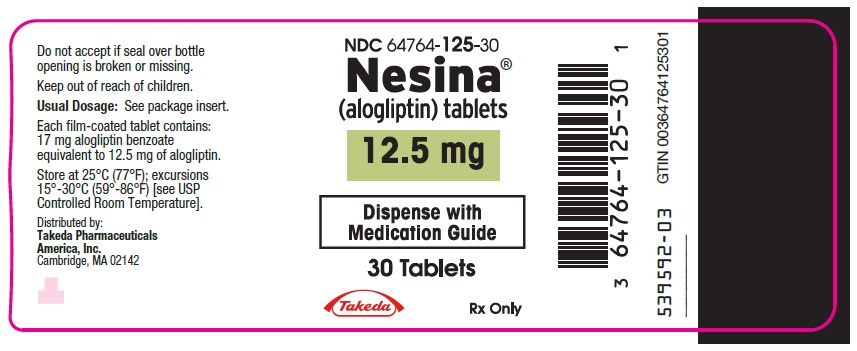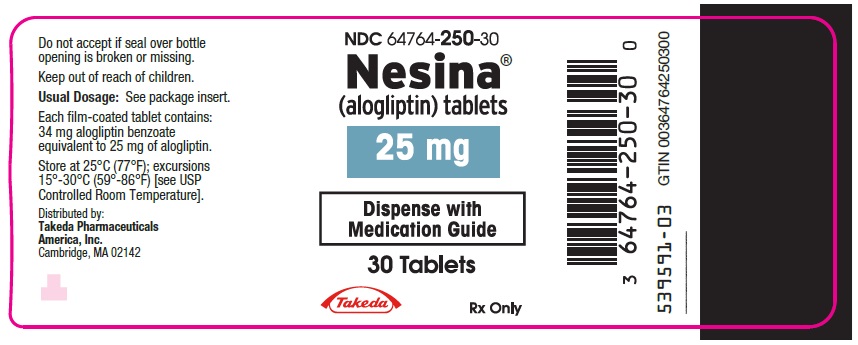 DRUG LABEL: Nesina
NDC: 64764-625 | Form: TABLET, FILM COATED
Manufacturer: Takeda Pharmaceuticals America, Inc.
Category: prescription | Type: HUMAN PRESCRIPTION DRUG LABEL
Date: 20250228

ACTIVE INGREDIENTS: ALOGLIPTIN BENZOATE 6.25 mg/1 1
INACTIVE INGREDIENTS: MANNITOL; MICROCRYSTALLINE CELLULOSE; HYDROXYPROPYL CELLULOSE (90000 WAMW); CROSCARMELLOSE SODIUM; MAGNESIUM STEARATE; HYPROMELLOSE 2910 (6 MPA.S); TITANIUM DIOXIDE; FERRIC OXIDE RED; POLYETHYLENE GLYCOL 8000; SHELLAC; FERROSOFERRIC OXIDE; BUTYL ALCOHOL; ALCOHOL

HIGHLIGHTS OF PRESCRIBING INFORMATION

These highlights do not include all the information needed to use NESINA® safely and effectively. See full prescribing information for NESINA.
NESINA (alogliptin) tablets, for oral use
Initial U.S. Approval: 2013

1 INDICATIONS AND USAGE

NESINA is a dipeptidyl peptidase-4 (DPP-4) inhibitor indicated as an adjunct to diet and exercise to improve glycemic control in adults with type 2 diabetes mellitus. (1)

Limitations of Use: Should not be used in patients with type 1 diabetes mellitus. (1)

2 DOSAGE AND ADMINISTRATION

- The recommended dosage in patients with normal renal function or mild renal impairment is 25 mg orally once daily. (2.1)
- Can be taken with or without food. (2.1)
- Adjust dosage if moderate or severe renal impairment or end-stage renal disease (ESRD). (2.2)

Degree of Renal Impairment | Creatinine Clearance (mL/min) | Recommended Dosage
Moderate | ≥30 to <60 | 12.5 mg once daily
Severe/ESRD | <30 | 6.25 mg once daily

3 DOSAGE FORMS AND STRENGTHS

Tablets: 25 mg, 12.5 mg and 6.25 mg (3)

4 CONTRAINDICATIONS

History of serious hypersensitivity to alogliptin or any of the excipients in NESINA. (4)

5 WARNINGS AND PRECAUTIONS

- Pancreatitis: There have been postmarketing reports of acute pancreatitis. If pancreatitis is suspected, promptly discontinue NESINA. (5.1)
- Heart failure: Consider the risks and benefits of NESINA prior to initiating treatment in patients at risk for heart failure. If heart failure develops, evaluate and manage according to current standards of care and consider discontinuation of NESINA. (5.2)
- Hypersensitivity: There have been postmarketing reports of serious hypersensitivity reactions in patients treated with NESINA such as anaphylaxis, angioedema and severe cutaneous adverse reactions, including Stevens-Johnson syndrome. If hypersensitivity reactions occur, discontinue NESINA, treat promptly, and monitor until signs and symptoms resolve. (5.3)
- Hepatic effects: Postmarketing reports of hepatic failure, sometimes fatal. Causality cannot be excluded. If liver injury is detected, promptly interrupt NESINA and assess patient for probable cause, then treat cause if possible, to resolution or stabilization. Do not restart NESINA if liver injury is confirmed and no alternative etiology can be found. (5.4)
- Hypoglycemia: Consider lowering the dosage of insulin secretagogue or insulin to reduce the risk of hypoglycemia when initiating NESINA. (5.5)
- Arthralgia: Severe and disabling arthralgia has been reported in patients taking DPP-4 inhibitors. Consider as a possible cause for severe joint pain and discontinue drug if appropriate. (5.6)
- Bullous pemphigoid: There have been postmarketing reports of bullous pemphigoid requiring hospitalization in patients taking DPP-4 inhibitors. Tell patients to report development of blisters or erosions. If bullous pemphigoid is suspected, discontinue NESINA. (5.7)

6 ADVERSE REACTIONS

Most common adverse reactions (incidence ≥4%) are nasopharyngitis, headache and upper respiratory tract infection. (6.1)

To report SUSPECTED ADVERSE REACTIONS, contact Takeda Pharmaceuticals America, Inc. at 1-877-TAKEDA-7 (1-877-825-3327) or FDA at 1-800-FDA-1088 or www.fda.gov/medwatch.

FULL PRESCRIBING INFORMATION

1 INDICATIONS AND USAGE

NESINA® is indicated as an adjunct to diet and exercise to improve glycemic control in adults with type 2 diabetes mellitus.

Limitations of Use

NESINA is not recommended for use in patients with type 1 diabetes mellitus.

2 DOSAGE AND ADMINISTRATION

2.1 Recommended Dosage

- The recommended dosage of NESINA is 25 mg taken orally once daily. Do not split tablets.
- NESINA may be taken with or without food [see Clinical Pharmacology (12.3)].
- Instruct patients if a dose is missed, not to double their next dose.

2.2 Patients with Renal Impairment

- Assess renal function prior to initiation of NESINA and periodically thereafter [see Use in Specific Populations (8.6)].
- No dose adjustment of NESINA is necessary for patients with mild renal impairment (creatinine clearance [CrCl] ≥60 mL/min).
- The dose of NESINA is 12.5 mg once daily for patients with moderate renal impairment (CrCl ≥30 to <60 mL/min).
- The dose of NESINA is 6.25 mg once daily for patients with severe renal impairment (CrCl ≥15 to <30 mL/min) or with end-stage renal disease (ESRD) (CrCl <15 mL/min or requiring hemodialysis). NESINA may be administered without regard to the timing of dialysis. NESINA has not been studied in patients undergoing peritoneal dialysis [see Use in Specific Populations (8.6), Clinical Pharmacology (12.3)].

3 DOSAGE FORMS AND STRENGTHS

- 25 mg tablets are light red, oval, biconvex, film-coated, with "TAK ALG-25" printed on one side.
- 12.5 mg tablets are yellow, oval, biconvex, film-coated, with "TAK ALG-12.5" printed on one side.
- 6.25 mg tablets are light pink, oval, biconvex, film-coated, with "TAK ALG-6.25" printed on one side.

4 CONTRAINDICATIONS

NESINA is contraindicated in patients with a history of serious hypersensitivity to alogliptin or any of the excipients in NESINA. Reactions such as anaphylaxis, angioedema and severe cutaneous adverse reactions have been reported [see Warnings and Precautions (5.3), Adverse Reactions (6.2)].

5 WARNINGS AND PRECAUTIONS

5.1 Pancreatitis

Acute pancreatitis has been reported in the postmarketing setting and in randomized clinical trials. In glycemic control trials in patients with type 2 diabetes mellitus, acute pancreatitis was reported in 6 (0.2%) patients treated with NESINA 25 mg and 2 (<0.1%) patients treated with active comparators or placebo. In the EXAMINE trial (a cardiovascular outcomes trial of patients with type 2 diabetes mellitus and high cardiovascular (CV) risk), acute pancreatitis was reported in 10 (0.4%) of patients treated with NESINA and in 7 (0.3%) of patients treated with placebo.

It is unknown whether patients with a history of pancreatitis are at increased risk for pancreatitis while using NESINA.

After initiation of NESINA, patients should be observed for signs and symptoms of pancreatitis. If pancreatitis is suspected, NESINA should promptly be discontinued and appropriate management should be initiated.

5.2 Heart Failure

In the EXAMINE trial which enrolled patients with type 2 diabetes mellitus and recent acute coronary syndrome, 106 (3.9%) of patients treated with NESINA and 89 (3.3%) of patients treated with placebo were hospitalized for congestive heart failure.

Consider the risks and benefits of NESINA prior to initiating treatment in patients at risk for heart failure, such as those with a prior history of heart failure and a history of renal impairment, and observe these patients for signs and symptoms of heart failure during therapy. Patients should be advised of the characteristic symptoms of heart failure and should be instructed to immediately report such symptoms. If heart failure develops, evaluate and manage according to current standards of care and consider discontinuation of NESINA.

5.3 Hypersensitivity Reactions

There have been postmarketing reports of serious hypersensitivity reactions in patients treated with NESINA [see Adverse Reactions (6.2)]. These reactions include anaphylaxis, angioedema and severe cutaneous adverse reactions, including Stevens-Johnson syndrome. If a serious hypersensitivity reaction is suspected, discontinue NESINA, assess for other potential causes for the event and institute alternative treatment for diabetes mellitus. Use caution in patients with a history of angioedema with another dipeptidyl peptidase-4 (DPP-4) inhibitor because it is unknown whether such patients will be predisposed to angioedema with NESINA.

5.4 Hepatic Effects

There have been postmarketing reports of fatal and nonfatal hepatic failure in patients taking NESINA, although some of the reports contain insufficient information necessary to establish the probable cause [see Adverse Reactions (6.2)].

In glycemic control trials in patients with type 2 diabetes mellitus, serum alanine aminotransferase (ALT) elevations greater than three times the upper limit of normal (ULN) were reported in 1.3% of patients treated with NESINA 25 mg and 1.7% of patients treated with active comparators or placebo. In the EXAMINE trial (a cardiovascular outcomes trial of patients with type 2 diabetes mellitus and high cardiovascular (CV) risk), increases in serum alanine aminotransferase three times the upper limit of the reference range occurred in 2.4% of patients treated with NESINA and in 1.8% of patients treated with placebo.

Measure liver tests promptly in patients who report symptoms that may indicate liver injury, including fatigue, anorexia, right upper abdominal discomfort, dark urine or jaundice. In this clinical context, if the patient is found to have clinically significant liver enzyme elevations and if abnormal liver tests persist or worsen, NESINA should be interrupted and investigation done to establish the probable cause. NESINA should not be restarted in these patients without another explanation for the liver test abnormalities.

5.5 Hypoglycemia with Concomitant Use with Insulin or Insulin Secretagogues

Insulin and insulin secretagogues, such as sulfonylureas, are known to cause hypoglycemia. Therefore, a lower dosage of insulin or insulin secretagogue may be required to minimize the risk of hypoglycemia when used in combination with NESINA.

5.6 Severe and Disabling Arthralgia

There have been postmarketing reports of severe and disabling arthralgia in patients taking DPP-4 inhibitors. The time to onset of symptoms following initiation of drug therapy varied from one day to years. Patients experienced relief of symptoms upon discontinuation of the medication. A subset of patients experienced a recurrence of symptoms when restarting the same drug or a different DPP-4 inhibitor. Consider DPP-4 inhibitors as a possible cause for severe joint pain and discontinue drug if appropriate.

5.7 Bullous Pemphigoid

Postmarketing cases of bullous pemphigoid requiring hospitalization have been reported with DPP-4 inhibitor use. In reported cases, patients typically recovered with topical or systemic immunosuppressive treatment and discontinuation of the DPP-4 inhibitor. Tell patients to report development of blisters or erosions while receiving NESINA. If bullous pemphigoid is suspected, NESINA should be discontinued and referral to a dermatologist should be considered for diagnosis and appropriate treatment.

6 ADVERSE REACTIONS

The following serious adverse reactions are described below or elsewhere in the prescribing information:

- Pancreatitis [see Warnings and Precautions (5.1)]
- Heart Failure [see Warnings and Precautions (5.2)]
- Hypersensitivity Reactions [see Warnings and Precautions (5.3)]
- Hepatic Effects [see Warnings and Precautions (5.4)]
- Severe and Disabling Arthralgia [see Warnings and Precautions (5.6)]
- Bullous Pemphigoid [see Warnings and Precautions (5.7)]

6.1 Clinical Trials Experience

Because clinical trials are conducted under widely varying conditions, adverse reaction rates observed in the clinical trials of a drug cannot be directly compared to rates in the clinical trials of another drug and may not reflect the rates observed in practice.

A total of 14,778 patients with type 2 diabetes mellitus participated in 14 randomized, double-blind, controlled clinical trials of whom 9,052 subjects were treated with NESINA, 3,469 subjects were treated with placebo and 2,257 were treated with an active comparator. The racial distribution of patients exposed to trial medication was 71% White, 17% Asian, 6% Black or African American, 2% American Indian or Alaska Native, 0% Native Hawaiian/Other Pacific Islander and 5% Multiracial or other racial groups. The ethnic distribution was 30% Hispanic or Latino and 70% was not Hispanic or Latino. The mean duration of diabetes mellitus was seven years, the mean body mass index (BMI) was 31 kg/m^2 (49% of patients had a BMI ≥30 kg/m^2), and the mean age was 58 years (26% of patients ≥65 years of age). The mean exposure to NESINA was 49 weeks with 3,348 subjects treated for more than one year.

In a pooled analysis of these 14 controlled clinical trials, the overall incidence of adverse reactions was 73% in patients treated with NESINA 25 mg compared to 75% with placebo and 70% with active comparator. Overall discontinuation of therapy due to adverse reactions was 6.8% with NESINA 25 mg compared to 8.4% with placebo or 6.2% with active comparator.

Adverse reactions reported in ≥4% of adult patients treated with NESINA 25 mg and more frequently than in patients who received placebo are summarized in Table 1.

Table 1. Adverse Reactions Reported in ≥4% of Adult Patients with Type 2 Diabetes Mellitus Treated with NESINA 25 mg and More Frequently Than in Patients Given Placebo in Pooled Trials
 | Number of Patients (%)
 | NESINA 25 mg | Placebo | Active Comparator
 | N=6447 | N=3469 | N=2257
Nasopharyngitis | 309 (5) | 152 (4) | 113 (5)
Upper Respiratory Tract Infection | 287 (4) | 121 (4) | 113 (5)
Headache | 278 (4) | 101 (3) | 121 (5)

Hypoglycemia

Hypoglycemic events were documented based upon a blood glucose value and/or clinical signs and symptoms of hypoglycemia.

In the monotherapy trial, the incidence of hypoglycemia was 1.5% in patients treated with NESINA compared to 1.6% with placebo. The use of NESINA as add-on therapy to glyburide or insulin did not increase the incidence of hypoglycemia compared to placebo. In a monotherapy trial comparing NESINA to a sulfonylurea in elderly patients, the incidence of hypoglycemia was 5.4% with NESINA compared to 26% with glipizide (Table 2).

Table 2. Incidence and Rate of Hypoglycemia [Adverse reactions of hypoglycemia were based on all reports of symptomatic and asymptomatic hypoglycemia; a concurrent glucose measurement was not required; intent-to-treat population] in Placebo and Active-Controlled Trials in Adults with Type 2 Diabetes Mellitus when NESINA Was Used as Add-On Therapy to Glyburide, Insulin, Metformin, Pioglitazone or Compared to Glipizide or Metformin
Add-On to Glyburide (26 Weeks) | NESINA 25 mg | Placebo
 | N=198 | N=99
Overall (%) | 19 (10) | 11 (11)
Severe (%) [Severe events of hypoglycemia were defined as those events requiring medical assistance or exhibiting depressed level or loss of consciousness or seizure] | 0 | 1 (1)
Add-On to Insulin (± Metformin) (26 Weeks) | NESINA 25 mg | Placebo
 | N=129 | N=129
Overall (%) | 35 (27) | 31 (24)
Severe (%) | 1 (1) | 2 (2)
Add-On to Metformin (26 Weeks) | NESINA 25 mg | Placebo
 | N=207 | N=104
Overall (%) | 0 | 3 (3)
Severe (%) | 0 | 0
Add-On to Pioglitazone (± Metformin or Sulfonylurea) (26 Weeks) | NESINA 25 mg | Placebo
 | N=199 | N=97
Overall (%) | 14 (7) | 5 (5)
Severe (%) | 0 | 1 (1)
Compared to Glipizide (52 Weeks) | NESINA 25 mg | Glipizide
 | N=222 | N=219
Overall (%) | 12 (5) | 57 (26)
Severe (%) | 0 | 3 (1)
Compared to Metformin (26 Weeks) | NESINA 25 mg | Metformin 500 mg twice daily
 | N=112 | N=109
Overall (%) | 2 (2) | 2 (2)
Severe (%) | 0 | 0
Add-On to Metformin Compared to Glipizide (52 Weeks) | NESINA 25 mg | Glipizide
 | N=877 | N=869
Overall (%) | 12 (1) | 207 (4)
Severe (%) | 0 | 4 (1)

In the EXAMINE trial, the incidence of investigator reported hypoglycemia was 6.7% in patients receiving NESINA and 6.5% in patients receiving placebo. Serious adverse reactions of hypoglycemia were reported in 0.8% of patients treated with NESINA and in 0.6% of patients treated with placebo.

Renal Impairment

In glycemic control trials in patients with type 2 diabetes mellitus, 3.4% of patients treated with NESINA and 1.3% of patients treated with placebo had renal function adverse reactions. The most commonly reported adverse reactions were renal impairment (0.5% for NESINA and 0.1% for active comparators or placebo), decreased creatinine clearance (1.6% for NESINA and 0.5% for active comparators or placebo) and increased blood creatinine (0.5% for NESINA and 0.3% for active comparators or placebo) [see Use in Specific Populations (8.6)].

In the EXAMINE trial of high CV risk type 2 diabetes mellitus patients, 23% of patients treated with NESINA and 21% of patients treated with placebo had an investigator reported renal impairment adverse reaction. The most commonly reported adverse reactions were renal impairment (7.7% for NESINA and 6.7% for placebo), decreased glomerular filtration rate (4.9% for NESINA and 4.3% for placebo) and decreased renal clearance (2.2% for NESINA and 1.8% for placebo). Laboratory measures of renal function were also assessed. Estimated glomerular filtration rate decreased by 25% or more in 21.1% of patients treated with NESINA and 18.7% of patients treated with placebo. Worsening of chronic kidney disease stage was seen in 16.8% of patients treated with NESINA and in 15.5% of patients treated with placebo.

6.2 Postmarketing Experience

The following adverse reactions have been identified during the postmarketing use of NESINA. Because these reactions are reported voluntarily from a population of uncertain size, it is not always possible to reliably estimate their frequency or establish a causal relationship to drug exposure.

Gastrointestinal Disorders: acute pancreatitis, diarrhea, constipation, nausea, ileus

Hepatobiliary Disorders: fulminant hepatic failure

Immune System Disorders: hypersensitivity reactions including anaphylaxis

Investigations: hepatic enzyme elevations

Musculoskeletal and Connective Tissue Disorders: severe and disabling arthralgia, rhabdomyolysis

Renal and Urinary Disorders: tubulointerstitial nephritis

Skin and Subcutaneous Tissue Disorders: angioedema, rash, urticaria and severe cutaneous adverse reactions including Stevens-Johnson syndrome, bullous pemphigoid

7 DRUG INTERACTIONS

7.1 Insulin Secretagogues and Insulin

Insulin and insulin secretagogues are known to cause hypoglycemia. Coadministration of NESINA with an insulin secretagogue (e.g., sulfonylurea) or insulin may require lower dosages of the insulin secretagogue and insulin to reduce the risk of hypoglycemia [see Warnings and Precautions (5.5)].

8 USE IN SPECIFIC POPULATIONS

8.1 Pregnancy

Risk Summary

Limited data with NESINA in pregnant women are not sufficient to determine a drug-associated risk for major birth defects or miscarriage. There are risks to the mother and fetus associated with poorly controlled diabetes mellitus in pregnancy [see Clinical Considerations].

No adverse developmental effects were observed when alogliptin was administered to pregnant rats and rabbits during organogenesis at exposures 180- and 149-times the 25 mg clinical dose, respectively, based on plasma drug exposure (AUC) [see Data].

The estimated background risk of major birth defects is 6-10% in women with pre-gestational diabetes mellitus with a HbA1c >7 and has been reported to be as high as 20-25% in women with HbA1c >10. The estimated background risk of miscarriage for the indicated population is unknown. In the U.S. general population, the estimated background risk of major birth defects and miscarriage in clinically recognized pregnancies is 2-4% and 15-20%, respectively.

Clinical Considerations

Disease-associated Maternal and/or Embryo/Fetal Risk

Poorly controlled diabetes mellitus in pregnancy increases the maternal risk for diabetic ketoacidosis, pre-eclampsia, spontaneous abortions, preterm delivery, and delivery complications. Poorly controlled diabetes mellitus increases the fetal risk for major birth defects, still birth, and macrosomia related morbidity.

Data

Animal Data

Alogliptin administered to pregnant rabbits and rats during the period of organogenesis did not cause adverse developmental effects at doses of up to 200 mg/kg and 500 mg/kg, or 149 times and 180 times, the 25 mg clinical dose, respectively, based on plasma drug exposure (AUC). Placental transfer of alogliptin into the fetus was observed following oral dosing to pregnant rats.

No adverse developmental outcomes were observed in offspring when alogliptin was administered to pregnant rats during gestation and lactation at doses up to 250 mg/kg (~95 times the 25 mg clinical dose, based on AUC).

8.2 Lactation

Risk Summary

There is no information regarding the presence of alogliptin in human milk, the effects on the breastfed infant, or the effects on milk production. Alogliptin is present in rat milk: however, due to species specific differences in lactation physiology, animal lactation data may not reliably predict levels in human milk. The developmental and health benefits of breastfeeding should be considered along with the mother's clinical need for NESINA and any potential adverse effects on the breastfed infant from NESINA or from the underlying maternal condition.

8.4 Pediatric Use

The safety and effectiveness of NESINA have not been established in pediatric patients.

Effectiveness of NESINA was not demonstrated in a 52 week, randomized, double-blind, placebo-controlled trial (NCT02856113) in 151 pediatric patients aged 10 to 17 years with inadequately controlled type 2 diabetes mellitus.

8.5 Geriatric Use

Of the total number of patients (N=9052) in clinical safety and efficacy trials treated with NESINA, 2,257 (24.9%) patients were 65 years and older and 386 (4.3%) patients were 75 years and older. No overall differences in safety or effectiveness were observed between patients 65 years and over and younger patients.

8.6 Renal Impairment

A total of 602 adult patients with moderate renal impairment (eGFR ≥30 and <60 mL/min/1.73 m^2) and 4 patients with severe renal impairment/end-stage renal disease (eGFR <30 mL/min/1.73 m^2 or <15 mL/min/1.73 m^2, respectively) at baseline were treated with NESINA in clinical trials in patients with type 2 diabetes mellitus.

In the EXAMINE trial of high CV risk type 2 diabetes mellitus patients, 694 patients had moderate renal impairment and 78 patients had severe renal impairment or end-stage renal disease at baseline.

The recommended dose is 12.5 mg once daily in patients with moderate renal impairment and 6.25 mg once daily in patients with severe renal impairment, as well as in patients with ESRD requiring dialysis. NESINA may be administered without regard to the timing of the dialysis.

8.7 Hepatic Impairment

No dose adjustments are required in patients with mild to moderate hepatic impairment (Child-Pugh Grade A and B) [see Clinical Pharmacology (12.3)]. NESINA has not been studied in patients with severe hepatic impairment (Child-Pugh Grade C). Use caution when administering NESINA to patients with liver disease [see Warnings and Precautions (5.4)].

10 OVERDOSAGE

In the event of an overdose, it is reasonable to institute the necessary clinical monitoring and supportive therapy as dictated by the patient's clinical status. Per clinical judgment, it may be reasonable to initiate removal of unabsorbed material from the gastrointestinal tract.

Alogliptin is minimally dialyzable; over a three-hour hemodialysis session, approximately 7% of the drug was removed. Therefore, hemodialysis is unlikely to be beneficial in an overdose situation. It is not known if NESINA is dialyzable by peritoneal dialysis.

In the event of an overdose, contact the Poison Help Line (1-800-222-1222) or a medical toxicologist for additional overdosage management recommendations.

11 DESCRIPTION

NESINA tablets contain the active ingredient alogliptin, which is a selective, orally bioavailable inhibitor of the enzymatic activity of DPP-4.

Chemically, alogliptin is prepared as a benzoate salt, which is identified as 2-({6-[(3R)-3-aminopiperidin-1-yl]-3-methyl-2,4-dioxo-3,4-dihydropyrimidin-1(2H)-yl}methyl)benzonitrile monobenzoate. It has a molecular formula of C18H21N5O2∙C7H6O2 and a molecular weight of 461.51 daltons. The structural formula is:

Alogliptin benzoate is a white to off-white crystalline powder containing one asymmetric carbon in the aminopiperidine moiety. It is soluble in dimethylsulfoxide, sparingly soluble in water and methanol, slightly soluble in ethanol and very slightly soluble in octanol and isopropyl acetate.

Each NESINA tablet contains 34 mg, 17 mg or 8.5 mg alogliptin benzoate, which is equivalent to 25 mg, 12.5 mg or 6.25 mg, respectively, of alogliptin and the following inactive ingredients: croscarmellose sodium, hydroxypropyl cellulose, magnesium stearate, mannitol, and microcrystalline cellulose. In addition, the film coating contains the following inactive ingredients: ferric oxide (red or yellow), hypromellose, polyethylene glycol, and titanium dioxide and is marked with printing ink (Gray F1).

12 CLINICAL PHARMACOLOGY

12.1 Mechanism of Action

Increased concentrations of the incretin hormones such as glucagon-like peptide-1 (GLP-1) and glucose-dependent insulinotropic polypeptide (GIP) are released into the bloodstream from the small intestine in response to meals. These hormones cause insulin release from the pancreatic beta cells in a glucose-dependent manner but are inactivated by the DPP-4 enzyme within minutes. GLP-1 also lowers glucagon secretion from pancreatic alpha cells, reducing hepatic glucose production. In patients with type 2 diabetes mellitus, concentrations of GLP-1 are reduced but the insulin response to GLP-1 is preserved. Alogliptin is a DPP-4 inhibitor that slows the inactivation of the incretin hormones, thereby increasing their bloodstream concentrations and reducing fasting and postprandial glucose concentrations in a glucose-dependent manner in patients with type 2 diabetes mellitus. Alogliptin selectively binds to and inhibits DPP-4 but not DPP-8 or DPP-9 activity in vitro at concentrations approximating therapeutic exposures.

12.2 Pharmacodynamics

Dose-Response Relationships

Single-dose administration of NESINA to healthy subjects resulted in a peak inhibition of DPP-4 within two to three hours after dosing. The peak inhibition of DPP-4 exceeded 93% across doses of 12.5 mg to 800 mg. Inhibition of DPP-4 remained above 80% at 24 hours for doses greater than or equal to 25 mg. Peak and total exposure over 24 hours to active GLP-1 were three- to four-fold greater with NESINA (at doses of 25 to 200 mg) than placebo. In a 16 week, double-blind, placebo-controlled study, NESINA 25 mg demonstrated decreases in postprandial glucagon while increasing postprandial active GLP-1 levels compared to placebo over an eight-hour period following a standardized meal. It is unclear how these findings relate to changes in overall glycemic control in patients with type 2 diabetes mellitus. In this study, NESINA 25 mg demonstrated decreases in two-hour postprandial glucose compared to placebo (-30 mg/dL versus 17 mg/dL, respectively).

Multiple-dose administration of alogliptin to patients with type 2 diabetes mellitus also resulted in a peak inhibition of DPP-4 within one to two hours and exceeded 93% across all doses (25 mg, 100 mg and 400 mg) after a single dose and after 14 days of once-daily dosing. At these doses of NESINA, inhibition of DPP-4 remained above 81% at 24 hours after 14 days of dosing.

Cardiac Electrophysiology

In a randomized, placebo-controlled, four-arm, parallel-group study, 257 subjects were administered either alogliptin 50 mg, alogliptin 400 mg, moxifloxacin 400 mg or placebo once daily for a total of seven days. No increase in corrected QT (QTc) was observed with either dose of alogliptin. At the 400 mg dose, peak alogliptin plasma concentrations were 19-fold higher than the peak concentrations following the maximum recommended clinical dose of 25 mg.

12.3 Pharmacokinetics

The pharmacokinetics of NESINA has been studied in healthy subjects and in patients with type 2 diabetes mellitus. The pharmacokinetics of NESINA was similar in healthy subjects and in patients with type 2 diabetes mellitus. After multiple-dose administration up to 400 mg for 14 days in patients with type 2 diabetes mellitus, accumulation of alogliptin was minimal with an increase in total [e.g., area under the plasma concentration curve (AUC)] and peak (i.e., Cmax) alogliptin exposures of 34% and 9%, respectively. Total and peak exposure to alogliptin increased proportionally across single doses and multiple doses of alogliptin ranging from 25 mg to 400 mg. The intersubject coefficient of variation for alogliptin AUC was 17%.

Absorption

After administration of single, oral doses up to 800 mg in healthy subjects, the peak plasma alogliptin concentration (median Tmax) occurred one to two hours after dosing. The absolute bioavailability of NESINA is approximately 100%.

Effect of Food

Administration of NESINA with a high-fat meal results in no significant change in total and peak exposure to alogliptin.

Distribution

Following a single, 12.5 mg intravenous infusion of alogliptin to healthy subjects, the volume of distribution during the terminal phase was 417 L, indicating that the drug is well distributed into tissues.

Alogliptin is 20% bound to plasma proteins.

Elimination

NESINA was eliminated with a mean terminal half-life (t1/2) of approximately 21 hours. The renal clearance of alogliptin (9.6 L/hr) indicates some active renal tubular secretion and systemic clearance was 14.0 L/hr.

Metabolism

Alogliptin does not undergo extensive metabolism and 60% to 71% of the dose is excreted as unchanged drug in the urine.

Two minor metabolites were detected following administration of an oral dose of [^14C] alogliptin, N-demethylated, M-I (less than 1% of the parent compound), and N-acetylated alogliptin, M-II (less than 6% of the parent compound). M-I is an active metabolite and is an inhibitor of DPP-4 similar to the parent molecule; M-II does not display any inhibitory activity toward DPP-4 or other DPP-related enzymes. In vitro data indicate that CYP2D6 and CYP3A4 contribute to the limited metabolism of alogliptin.

Alogliptin exists predominantly as the (R)-enantiomer (more than 99%) and undergoes little or no chiral conversion in vivo to the (S)-enantiomer. The (S)-enantiomer is not detectable at the 25 mg dose.

Excretion

The primary route of elimination of [^14C] alogliptin-derived radioactivity occurs via renal excretion (76%) with 13% recovered in the feces, achieving a total recovery of 89% of the administered radioactive dose.

Specific Populations

Geriatric Patients

Age (18 to 80 years old) did not have any clinically meaningful effect on the pharmacokinetics of alogliptin.

Male and Female Patients

Gender did not have any clinically meaningful effect on the pharmacokinetics of alogliptin.

Racial or Ethnic Groups

Race (White, Black or African American and Asian) did not have any clinically meaningful effect on the pharmacokinetics of alogliptin.

Patients with Renal Impairment

A single-dose, open-label study was conducted to evaluate the pharmacokinetics of alogliptin 50 mg in patients with chronic renal impairment compared with healthy subjects. In patients with mild renal impairment (creatinine clearance [CrCl] ≥60 to <90 mL/min), an approximate 1.2-fold increase in plasma AUC of alogliptin was observed. In patients with moderate renal impairment (CrCl ≥30 to <60 mL/min), an approximate two-fold increase in plasma AUC of alogliptin was observed. In patients with severe renal impairment (CrCl ≥15 to <30 mL/min) and end-stage renal disease (ESRD) (CrCl <15 mL/min or requiring dialysis), an approximate three- and four-fold increase in plasma AUC of alogliptin were observed, respectively. Dialysis removed approximately 7% of the drug during a three-hour dialysis session [see Dosage and Administration (2.2), Use in Specific Populations (8.6)].

Patients with Hepatic Impairment

Total exposure to alogliptin was approximately 10% lower and peak exposure was approximately 8% lower in patients with moderate hepatic impairment (Child-Pugh Grade B) compared to healthy subjects. The magnitude of these reductions is not considered to be clinically meaningful. Patients with severe hepatic impairment (Child-Pugh Grade C) have not been studied [see Use in Specific Populations (8.7), Warnings and Precautions (5.4)].

Drug Interaction Studies

Clinical Studies

Effects of Alogliptin on the Pharmacokinetics of Other Drugs

In clinical studies, alogliptin did not meaningfully increase the systemic exposure to the following drugs that are metabolized by CYP isozymes or excreted unchanged in urine (Figure 1). No dose adjustment of NESINA is recommended based on results of the described pharmacokinetic studies.

Figure 1. Effect of Alogliptin on the Pharmacokinetic Exposure to Other Drugs

* Warfarin was given once daily at a stable dose in the range of 1 mg to 10 mg. Alogliptin had no significant effect on the prothrombin time (PT) or International Normalized Ratio (INR).

** Caffeine (1A2 substrate), tolbutamide (2C9 substrate), dextromethorphan (2D6 substrate), midazolam (3A4 substrate) and fexofenadine (P-gp substrate) were administered as a cocktail.

Effects of Other Drugs on the Pharmacokinetics of Alogliptin

There are no clinically meaningful changes in the pharmacokinetics of alogliptin when NESINA is administered concomitantly with the drugs described below (Figure 2).

Figure 2. Effect of Other Drugs on the Pharmacokinetic Exposure of Alogliptin

In Vitro Studies

Effect of Alogliptin on CYP Enzymes

Alogliptin is neither an inducer of CYP1A2, CYP2B6, CYP2C9, CYP2C19 and CYP3A4, nor an inhibitor of CYP1A2, CYP2C8, CYP2C9, CYP2C19, CYP3A4 and CYP2D6 at clinically relevant concentrations.

13 NONCLINICAL TOXICOLOGY

13.1 Carcinogenesis, Mutagenesis, Impairment of Fertility

Carcinogenesis

Rats were administered oral doses of 75, 400 and 800 mg/kg alogliptin for two years. No drug-related tumors were observed up to 75 mg/kg or approximately 32 times the maximum recommended clinical dose of 25 mg, based on area under the plasma concentration curve (AUC) exposure. At higher doses (approximately 308 times the maximum recommended clinical dose of 25 mg), a combination of thyroid C-cell adenomas and carcinomas increased in male but not female rats. No drug-related tumors were observed in mice after administration of 50, 150 or 300 mg/kg alogliptin for two years, or up to approximately 51 times the maximum recommended clinical dose of 25 mg, based on AUC exposure.

Mutagenesis

Alogliptin was not mutagenic or clastogenic, with and without metabolic activation, in the Ames test with S. typhimurium and E. coli or the cytogenetic assay in mouse lymphoma cells. Alogliptin was negative in the in vivo mouse micronucleus study.

Impairment of Fertility

In a fertility study in rats, alogliptin had no adverse effects on early embryonic development, mating or fertility at doses up to 500 mg/kg, or approximately 172 times the clinical dose based on plasma drug exposure (AUC).

14 CLINICAL STUDIES

14.1 Overview of Clinical Trials in Adults with Type 2 Diabetes Mellitus

NESINA has been studied as monotherapy and in combination with metformin, a sulfonylurea, a thiazolidinedione (either alone or in combination with metformin or a sulfonylurea) and insulin (either alone or in combination with metformin).

A total of 14,053 patients with type 2 diabetes mellitus were randomized in 11 double-blind, placebo- or active-controlled clinical safety and efficacy trials conducted to evaluate the effects of NESINA on glycemic control. The racial distribution of patients exposed to trial medication was 70% White, 17% Asian, 6% Black or African American, 2% American Indian or Alaska Native, 0% Native Hawaiian/Other Pacific Islander and 5% Multiracial or other racial groups. The ethnic distribution was 30% Hispanic or Latino. Patients had an overall mean age of 57 years (range 21 to 91 years).

In patients with type 2 diabetes mellitus, treatment with NESINA produced clinically meaningful and statistically significant improvements in hemoglobin A1c (A1C) compared to placebo. As is typical for trials of agents to treat type 2 diabetes mellitus, the mean reduction in A1C with NESINA appears to be related to the degree of A1C elevation at baseline.

NESINA had similar changes from baseline in serum lipids compared to placebo.

14.2 Patients with Inadequate Glycemic Control on Diet and Exercise

A total of 1,768 patients with type 2 diabetes mellitus participated in three double-blind trials to evaluate the efficacy and safety of NESINA in patients with inadequate glycemic control on diet and exercise. All three trials had a four week, single-blind, placebo run-in period followed by a 26 week randomized treatment period. Patients who failed to meet prespecified hyperglycemic goals during the 26 week treatment periods received glycemic rescue therapy.

In a 26 week, double-blind, placebo-controlled trial, a total of 329 patients (mean baseline A1C = 8%) were randomized to receive NESINA 12.5 mg, NESINA 25 mg or placebo once daily. Treatment with NESINA 25 mg resulted in statistically significant improvements from baseline in A1C and fasting plasma glucose (FPG) compared to placebo at Week 26 (Table 3). A total of 8% of patients receiving NESINA 25 mg and 30% of those receiving placebo required glycemic rescue therapy.

Improvements in A1C were not affected by gender, age or baseline body mass index (BMI).

The mean change in body weight with NESINA was similar to placebo.

Table 3. Glycemic Parameters at Week 26 in a Placebo-Controlled Monotherapy Trial of NESINA [Intent-to-treat population using last observation in the trial]
 | NESINA 25 mg | Placebo
A1C (%) | N=128 | N=63
Baseline (mean) | 7.9 | 8.0
Change from baseline (adjusted mean [Least squares means adjusted for treatment, baseline value, geographic region and duration of diabetes mellitus]) | -0.6 | 0
Difference from placebo (adjusted mean with 95% confidence interval) | -0.6 [p<0.01 compared to placebo] (-0.8, -0.3) | ˗
% of patients (n/N) achieving A1C ≤7% | 44% (58/131) | 23% (15/64)
FPG (mg/dL) | N=129 | N=64
Baseline (mean) | 172 | 173
Change from baseline (adjusted mean) | -16 | 11
Difference from placebo (adjusted mean with 95% confidence interval) | -28 (-40, -15) | ˗

In a 26 week, double-blind, active-controlled trial, a total of 655 patients (mean baseline A1C = 8.8%) were randomized to receive NESINA 25 mg alone, pioglitazone 30 mg alone, NESINA 12.5 mg with pioglitazone 30 mg or NESINA 25 mg with pioglitazone 30 mg once daily. Coadministration of NESINA 25 mg with pioglitazone 30 mg resulted in statistically significant improvements from baseline in A1C and FPG compared to NESINA 25 mg alone and to pioglitazone 30 mg alone (Table 4). A total of 3% of patients receiving NESINA 25 mg coadministered with pioglitazone 30 mg, 11% of those receiving NESINA 25 mg alone and 6% of those receiving pioglitazone 30 mg alone required glycemic rescue.

Improvements in A1C were not affected by gender, age or baseline BMI.

The mean increase in body weight was similar between pioglitazone alone and NESINA when coadministered with pioglitazone.

Table 4. Glycemic Parameters at Week 26 in an Active-Controlled Trial of NESINA, Pioglitazone, and NESINA in Combination with Pioglitazone [Intent-to-treat population using last observation carried forward]
 | NESINA 25 mg | Pioglitazone 30 mg | NESINA 25 mg + Pioglitazone 30 mg
A1C (%) | N=160 | N=153 | N=158
Baseline (mean) | 8.8 | 8.8 | 8.8
Change from baseline (adjusted mean [Least squares means adjusted for treatment, geographic region and baseline value]) | -1.0 | -1.2 | -1.7
Difference from NESINA 25 mg (adjusted mean with 95% confidence interval) | ˗ | ˗ | -0.8 [p<0.01 compared to NESINA 25 mg or pioglitazone 30 mg] (-1.0, -0.5)
Difference from pioglitazone 30 mg (adjusted mean with 95% confidence interval) | ˗ | ˗ | -0.6 (-0.8, -0.3)
% of patients (n/N) achieving A1C ≤7% | 24% (40/164) | 34% (55/163) | 63% (103/164)
FPG (mg/dL) | N=162 | N=157 | N=162
Baseline (mean) | 189 | 189 | 185
Change from baseline (adjusted mean) | -26 | -37 | -50
Difference from NESINA 25 mg (adjusted mean with 95% confidence interval) | ˗ | ˗ | -24 (-34, -15)
Difference from pioglitazone 30 mg (adjusted mean with 95% confidence interval) | ˗ | ˗ | -13 (-22, -4)

In a 26 week, double-blind, placebo-controlled trial, a total of 784 patients inadequately controlled on diet and exercise alone (mean baseline A1C = 8.4%) were randomized to one of seven treatment groups: placebo; metformin HCl 500 mg or metformin HCl 1000 mg twice daily; NESINA 12.5 mg twice daily; NESINA 25 mg daily; or NESINA 12.5 mg in combination with metformin HCl 500 mg or metformin HCl 1000 mg twice daily. Both coadministration treatment arms (NESINA 12.5 mg + metformin HCl 500 mg and NESINA 12.5 mg + metformin HCl 1000 mg) resulted in statistically significant improvements in A1C and FPG when compared with their respective individual alogliptin and metformin component regimens (Table 5). Coadministration treatment arms demonstrated improvements in two hour postprandial glucose (PPG) compared to NESINA alone or metformin alone (Table 5). A total of 12.3% of patients receiving NESINA 12.5 mg + metformin HCl 500 mg, 2.6% of patients receiving NESINA 12.5 mg + metformin HCl 1000 mg, 17.3% of patients receiving NESINA 12.5 mg, 22.9% of patients receiving metformin HCl 500 mg, 10.8% of patients receiving metformin HCl 1000 mg and 38.7% of patients receiving placebo required glycemic rescue.

Improvements in A1C were not affected by gender, age, race or baseline BMI. The mean decrease in body weight was similar between metformin alone and NESINA when coadministered with metformin.

Table 5. Glycemic Parameters at Week 26 for NESINA and Metformin Alone and in Combination in Adult Patients with Type 2 Diabetes Mellitus
 | Placebo | NESINA 12.5 mg Twice Daily | Metformin HCl 500 mg Twice Daily | Metformin HCl 1000 mg Twice Daily | NESINA 12.5 mg + Metformin HCl 500 mg Twice Daily | NESINA 12.5 mg + Metformin HCl 1000 mg Twice Daily
A1C (%) [Intent-to-treat population using last observation on trial prior to discontinuation of double-blind trial medication or sulfonylurea rescue therapy for patients needing rescue] | N=102 | N=104 | N=103 | N=108 | N=102 | N=111
Baseline (mean) | 8.5 | 8.4 | 8.5 | 8.4 | 8.5 | 8.4
Change from baseline (adjusted mean [Least squares means adjusted for treatment, geographic region and baseline value]) | 0.1 | -0.6 | -0.7 | -1.1 | -1.2 | -1.6
Difference from metformin (adjusted mean with 95% confidence interval) | - | - | - | - | -0.6 [p<0.05 when compared to metformin and NESINA alone] (-0.9, -0.3) | -0.4 (-0.7, -0.2)
Difference from NESINA (adjusted mean with 95% confidence interval) | - | - | - | - | -0.7 (-1.0, -0.4) | -1.0 (-1.3, -0.7)
% of patients (n/N) achieving A1C <7% [Compared using logistic regression] | 4% (4/102) | 20% (21/104) | 27% (28/103) | 34% (37/108) | 47% (48/102) | 59% (66/111)
FPG (mg/dL) | N=105 | N=106 | N=106 | N=110 | N=106 | N=112
Baseline (mean) | 187 | 177 | 180 | 181 | 176 | 185
Change from baseline (adjusted mean) | 12 | -10 | -12 | -32 | -32 | -46
Difference from metformin (adjusted mean with 95% confidence interval) | - | - | - | - | -20 (-33, -8) | -14 (-26, -2)
Difference from NESINA (adjusted mean with 95% confidence interval) | - | - | - | - | -22 (-35, -10) | -36 (-49, -24)
2-Hour PPG (mg/dL) [Intent-to-treat population using data available at Week 26] | N=26 | N=34 | N=28 | N=37 | N=31 | N=37
Baseline (mean) | 263 | 272 | 247 | 266 | 261 | 268
Change from baseline (adjusted mean) | -21 | -43 | -49 | -54 | -68 | -86
Difference from metformin (adjusted mean with 95% confidence interval) | - | - | - | - | -19 (-49, 11) | -32 (-58, -5)
Difference from NESINA (adjusted mean with 95% confidence interval) | - | - | - | - | -25 (-53, -3) | -43 (-70, -16)

14.3 Combination Therapy

Add-On Therapy to Metformin

A total of 2081 patients with type 2 diabetes mellitus participated in two 26 week, double-blind, placebo-controlled trials to evaluate the efficacy and safety of NESINA as add-on therapy to metformin. In both trials, patients were inadequately controlled on metformin at a dose of at least 1500 mg per day or at the maximum tolerated dose. All patients entered a four week, single-blind placebo run-in period prior to randomization. Patients who failed to meet prespecified hyperglycemic goals during the 26 week treatment periods received glycemic rescue therapy.

In the first 26 week, placebo-controlled trial, a total of 527 patients already on metformin (mean baseline A1C = 8%) were randomized to receive NESINA 12.5 mg, NESINA 25 mg or placebo. Patients were maintained on a stable dose of metformin (median dose = 1700 mg) during the treatment period. NESINA 25 mg in combination with metformin resulted in statistically significant improvements from baseline in A1C and FPG at Week 26, when compared to placebo (Table 6). A total of 8% of patients receiving NESINA 25 mg and 24% of patients receiving placebo required glycemic rescue.

Improvements in A1C were not affected by gender, age, baseline BMI or baseline metformin dose.

The mean decrease in body weight was similar between NESINA and placebo when given in combination with metformin.

Table 6. Glycemic Parameters at Week 26 in a Placebo-Controlled Trial of NESINA as Add-On Therapy to Metformin in Adults with Type 2 Diabetes Mellitus [Intent-to-treat population using last observation on trial]
 | NESINA 25 mg + Metformin | Placebo + Metformin
A1C (%) | N=203 | N=103
Baseline (mean) | 7.9 | 8.0
Change from baseline (adjusted mean [Least squares means adjusted for treatment, baseline value, geographic region and baseline metformin dose]) | -0.6 | -0.1
Difference from placebo (adjusted mean with 95% confidence interval) | -0.5 [p<0.001 compared to placebo] (-0.7, -0.3) | ˗
% of patients (n/N) achieving A1C ≤7% | 44% (92/207) | 18% (19/104)
FPG (mg/dL) | N=204 | N=104
Baseline (mean) | 172 | 180
Change from baseline (adjusted mean) | -17 | 0
Difference from placebo (adjusted mean with 95% confidence interval) | -17 (-26, -9) | ˗

In the second 26 week, double-blind, placebo-controlled trial, a total of 1,554 patients already on metformin (mean baseline A1C = 8.5%) were randomized to one of 12 double-blind treatment groups: placebo; 12.5 mg or 25 mg of NESINA alone; 15 mg, 30 mg or 45 mg of pioglitazone alone; or 12.5 mg or 25 mg of NESINA in combination with 15 mg, 30 mg or 45 mg of pioglitazone. Patients were maintained on a stable dose of metformin (median dose = 1700 mg) during the treatment period. Coadministration of NESINA and pioglitazone provided statistically significant improvements in A1C and FPG compared to placebo, to NESINA alone or to pioglitazone alone when added to background metformin therapy (Table 7, Figure 3). In addition, improvements from baseline A1C were comparable between NESINA alone and pioglitazone alone (15 mg, 30 mg and 45 mg) at Week 26. A total of 4%, 5% or 2% of patients receiving NESINA 25 mg with 15 mg, 30 mg or 45 mg pioglitazone, 33% of patients receiving placebo, 13% of patients receiving NESINA 25 mg and 10%, 15% or 9% of patients receiving pioglitazone 15 mg, 30 mg or 45 mg alone required glycemic rescue.

Improvements in A1C were not affected by gender, age or baseline BMI.

The mean increase in body weight was similar between pioglitazone alone and NESINA when coadministered with pioglitazone.

Table 7. Glycemic Parameters in a 26 Week Trial of NESINA, Pioglitazone and NESINA in Combination with Pioglitazone when Added to Metformin in Adults with Type 2 Diabetes Mellitus [Intent-to-treat population using last observation in the trial]
 | Placebo | NESINA 25 mg | Pioglitazone 15 mg | Pioglitazone 30 mg | Pioglitazone 45 mg | NESINA 25 mg + Pioglitazone 15 mg | NESINA 25 mg + Pioglitazone 30 mg | NESINA 25 mg + Pioglitazone 45 mg
A1C (%) | N=126 | N=123 | N=127 | N=123 | N=126 | N=127 | N=124 | N=126
Baseline (mean) | 8.5 | 8.6 | 8.5 | 8.5 | 8.5 | 8.5 | 8.5 | 8.6
Change from baseline (adjusted mean [Least squares means adjusted for treatment, geographic region, metformin dose and baseline value]) | -0.1 | -0.9 | -0.8 | -0.9 | -1.0 | -1.3 [p≤0.01 when compared to corresponding doses of pioglitazone and NESINA alone] | -1.4 | -1.6
Difference from pioglitazone (adjusted mean with 95% confidence interval) | - | - | - | - |  | -0.5 (-0.7, -0.3) | -0.5 (-0.7, -0.3) | -0.6 (-0.8, -0.4)
Difference from NESINA (adjusted mean with 95% confidence interval) | - | - | - | - | - | -0.4 (-0.6, -0.1) | -0.5 (-0.7, -0.3) | -0.7 (-0.9, -0.5)
Patients (%) achieving A1C ≤7% | 6% (8/129) | 27% (35/129) | 26% (33/129) | 30% (38/129) | 36% (47/129) | 55% (71/130) | 53% (69/130) | 60% (78/130)
FPG (mg/dL) | N=129 | N=126 | N=127 | N=125 | N=129 | N=130 | N=126 | N=127
Baseline (mean) | 177 | 184 | 177 | 175 | 181 | 179 | 179 | 178
Change from baseline (adjusted mean) | 7 | -19 | -24 | -29 | -32 | -38 | -42 | -53
Difference from pioglitazone (adjusted mean with 95% confidence interval) | - | - | - | - | - | -14 (-24, -5) | -13 (-23, -3) | -20 (-30, -11)
Difference from NESINA (adjusted mean with 95% confidence interval) | - | - | - | - | - | -19 (-29, -10) | -23 (-33, -13) | -34 (-44, -24)

Figure 3. Change from Baseline in A1C at Week 26 with NESINA and Pioglitazone Alone and NESINA in Combination with Pioglitazone When Added to Metformin in Adults with Type 2 Diabetes Mellitus

Add-On Therapy to a Thiazolidinedione

In a 26 week, placebo-controlled trial, a total of 493 patients inadequately controlled on a thiazolidinedione alone or in combination with metformin or a sulfonylurea (10 mg) (mean baseline A1C = 8%) were randomized to receive NESINA 12.5 mg, NESINA 25 mg or placebo. Patients were maintained on a stable dose of pioglitazone (median dose = 30 mg) during the treatment period; those who were also previously treated on metformin (median dose = 2000 mg) or sulfonylurea (median dose = 10 mg) prior to randomization were maintained on the combination therapy during the treatment period. All patients entered into a four week, single-blind placebo run-in period prior to randomization. Patients who failed to meet prespecified hyperglycemic goals during the 26 week treatment period received glycemic rescue therapy.

The addition of NESINA 25 mg once daily to pioglitazone therapy resulted in statistically significant improvements from baseline in A1C and FPG at Week 26, compared to placebo (Table 8). A total of 9% of patients who were receiving NESINA 25 mg and 12% of patients receiving placebo required glycemic rescue.

Improvements in A1C were not affected by gender, age, baseline BMI or baseline pioglitazone dose.

Clinically meaningful reductions in A1C were observed with NESINA compared to placebo regardless of whether subjects were receiving concomitant metformin or sulfonylurea (-0.2% placebo versus -0.9% NESINA) therapy or pioglitazone alone (0% placebo versus -0.52% NESINA).

The mean increase in body weight was similar between NESINA and placebo when given in combination with pioglitazone.

Table 8. Glycemic Parameters in a 26 Week, Placebo-Controlled Trial of NESINA as Add-On Therapy to Pioglitazone in Adults with Type 2 Diabetes Mellitus [Intent-to-treat population using last observation on trial]
 | NESINA 25 mg + Pioglitazone ± Metformin ± Sulfonylurea | Placebo + Pioglitazone ± Metformin ± Sulfonylurea
A1C (%) | N=195 | N=95
Baseline (mean) | 8 | 8
Change from baseline (adjusted mean [Least squares means adjusted for treatment, baseline value, geographic region, baseline treatment regimen (pioglitazone, pioglitazone + metformin or pioglitazone + sulfonylurea) and baseline pioglitazone dose]) | -0.8 | -0.2
Difference from placebo (adjusted mean with 95% confidence interval) | -0.6 [p<0.01 compared to placebo] (-0.8, -0.4) | ˗
% of patients (n/N) achieving A1C ≤7% | 49% (98/199) | 34% (33/97)
FPG (mg/dL) | N=197 | N=97
Baseline (mean) | 170 | 172
Change from baseline (adjusted mean) | -20 | -6
Difference from placebo (adjusted mean with 95% confidence interval) | -14 (-23, -5) | ˗

Add-on Combination Therapy with Pioglitazone and Metformin

In a 52 week, active-comparator trial, a total of 803 patients inadequately controlled (mean baseline A1C = 8.2%) on a current regimen of pioglitazone 30 mg and metformin at least 1500 mg per day or at the maximum tolerated dose were randomized to either receive the addition of NESINA 25 mg or the titration of pioglitazone 30 mg to 45 mg following a four week, single-blind placebo run-in period. Patients were maintained on a stable dose of metformin (median dose = 1700 mg). Patients who failed to meet prespecified hyperglycemic goals during the 52 week treatment period received glycemic rescue therapy.

In combination with pioglitazone and metformin, NESINA 25 mg was shown to be statistically superior in lowering A1C and FPG compared with the titration of pioglitazone from 30 mg to 45 mg at Week 26 and at Week 52 (Table 9; results shown only for Week 52). A total of 11% of patients in the NESINA 25 mg treatment group and 22% of patients in the pioglitazone up-titration group required glycemic rescue.

Improvements in A1C were not affected by gender, age, race or baseline BMI.

The mean increase in body weight was similar in both treatment arms.

Table 9. Glycemic Parameters in a 52 Week, Active-Controlled Trial of NESINA as Add-On Combination Therapy to Metformin and Pioglitazone in Adults with Type 2 Diabetes Mellitus [Intent-to-treat population using last observation in the trial]
 | NESINA 25 mg + Pioglitazone 30 mg + Metformin | Pioglitazone 45 mg + Metformin
A1C (%) | N=397 | N=394
Baseline (mean) | 8.2 | 8.1
Change from baseline (adjusted mean [Least squares means adjusted for treatment, baseline value, geographic region and baseline metformin dose]) | -0.7 | -0.3
Difference from pioglitazone 45 mg + metformin (adjusted mean with 95% confidence interval) | -0.4 [Noninferior and statistically superior to metformin + pioglitazone at the 0.025 one-sided significance level] (-0.5, -0.3) | ˗
% of patients (n/N) achieving A1C≤7% | 33% (134/404) [p<0.001 compared to pioglitazone 45 mg + metformin] | 21% (85/399)
Fasting Plasma Glucose (mg/dL) | N=399 | N=396
Baseline (mean) | 162 | 162
Change from baseline (adjusted mean) | -15 | -4
Difference from pioglitazone 45 mg + metformin (adjusted mean with 95% confidence interval) | -11 (-16, -6) | ˗

Add-On Therapy to a Sulfonylurea

In a 26 week, placebo-controlled trial, a total of 500 patients inadequately controlled on a sulfonylurea (mean baseline A1C = 8.1%) were randomized to receive NESINA 12.5 mg, NESINA 25 mg or placebo. Patients were maintained on a stable dose of glyburide (median dose = 10 mg) during the treatment period. All patients entered into a four week, single-blind, placebo run-in period prior to randomization. Patients who failed to meet prespecified hyperglycemic goals during the 26 week treatment period received glycemic rescue therapy.

The addition of NESINA 25 mg to glyburide therapy resulted in statistically significant improvements from baseline in A1C at Week 26 when compared to placebo (Table 10). Improvements in FPG observed with NESINA 25 mg were not statistically significant compared with placebo. A total of 16% of patients receiving NESINA 25 mg and 28% of those receiving placebo required glycemic rescue.

Improvements in A1C were not affected by gender, age, baseline BMI or baseline glyburide dose.

The mean change in body weight was similar between NESINA and placebo when given in combination with glyburide.

Table 10. Glycemic Parameters in a 26 Week, Placebo-Controlled Trial of NESINA as Add-On Therapy to Glyburide in Adults with Type 2 Diabetes Mellitus [Intent-to-treat population using last observation on trial]
 | NESINA 25 mg + Glyburide | Placebo + Glyburide
A1C (%) | N=197 | N=97
Baseline (mean) | 8.1 | 8.2
Change from baseline (adjusted mean [Least squares means adjusted for treatment, baseline value, geographic region and baseline glyburide dose]) | -0.5 | 0
Difference from placebo (adjusted mean with 95% confidence interval) | -0.5 [p<0.01 compared to placebo] (-0.7, -0.3) | ˗
% of patients (n/N) achieving A1C ≤7% | 35% (69/198) | 18% (18/99)
FPG (mg/dL) | N=198 | N=99
Baseline (mean) | 174 | 177
Change from baseline (adjusted mean) | -8 | 2
Difference from placebo (adjusted mean with 95% confidence interval) | -11 (-22, 1) | ˗

Add-On Therapy to Insulin

In a 26 week, placebo-controlled trial, a total of 390 patients inadequately controlled on insulin alone (42%) or in combination with metformin (58%) (mean baseline A1C = 9.3%) were randomized to receive NESINA 12.5 mg, NESINA 25 mg or placebo. Patients were maintained on their insulin regimen (median dose = 55 IU) upon randomization and those previously treated with insulin in combination with metformin (median dose = 1700 mg) prior to randomization continued on the combination regimen during the treatment period. Patients entered the trial on short-, intermediate- or long-acting (basal) insulin or premixed insulin. Patients who failed to meet prespecified hyperglycemic goals during the 26 week treatment period received glycemic rescue therapy.

The addition of NESINA 25 mg once daily to insulin therapy resulted in statistically significant improvements from baseline in A1C and FPG at Week 26, when compared to placebo (Table 11). A total of 20% of patients receiving NESINA 25 mg and 40% of those receiving placebo required glycemic rescue.

Improvements in A1C were not affected by gender, age, baseline BMI or baseline insulin dose. Clinically meaningful reductions in A1C were observed with NESINA compared to placebo regardless of whether subjects were receiving concomitant metformin and insulin (-0.2% placebo versus -0.8% NESINA) therapy or insulin alone (0.1% placebo versus -0.7% NESINA).

The mean increase in body weight was similar between NESINA and placebo when given in combination with insulin.

Table 11. Glycemic Parameters in a 26 Week, Placebo-Controlled Trial of NESINA as Add-On Therapy to Insulin in Adults with Type 2 Diabetes Mellitus [Intent-to-treat population using last observation in the trial]
 | NESINA 25 mg + Insulin ± Metformin | Placebo + Insulin ± Metformin
A1C (%) | N=126 | N=126
Baseline (mean) | 9.3 | 9.3
Change from baseline (adjusted mean [Least squares means adjusted for treatment, baseline value, geographic region, baseline treatment regimen (insulin or insulin + metformin) and baseline daily insulin dose]) | -0.7 | -0.1
Difference from placebo (adjusted mean with 95% confidence interval) | -0.6 [p<0.05 compared to placebo] (-0.8, -0.4) | ˗
% of patients (n/N) achieving A1C ≤7% | 8% (10/129) | 1% (1/129)
FPG (mg/dL) | N=128 | N=127
Baseline (mean) | 186 | 196
Change from baseline (adjusted mean) | -12 | 6
Difference from placebo (adjusted mean with 95% confidence interval) | -18 (-33, -2) | ˗

14.4 Cardiovascular Safety Trial

A randomized, double-blind, placebo-controlled cardiovascular outcomes trial (EXAMINE) was conducted to evaluate the cardiovascular risk of NESINA. The trial compared the risk of major adverse cardiovascular events (MACE) between NESINA (N=2701) and placebo (N=2679) when added to standard of care therapies for diabetes mellitus and atherosclerotic vascular disease (ASCVD). The trial was event driven and patients were followed until a sufficient number of primary outcome events accrued.

Eligible patients were adults with type 2 diabetes mellitus who had inadequate glycemic control at baseline (e.g., HbA1c >6.5%) and had been hospitalized for an acute coronary syndrome event (e.g., acute myocardial infarction or unstable angina requiring hospitalization) 15 to 90 days prior to randomization. The dose of NESINA was based on estimated renal function at baseline per dosage and administration recommendations [see Dosage and Administration (2.2)]. The average time between an acute coronary syndrome event and randomization was approximately 48 days.

The mean age of the population was 61 years. Most patients were male (68%), White (73%), and were recruited from outside of the United States (86%). Asian and Black or African American patients contributed 20% and 4% of the total population, respectively. At the time of randomization patients had a diagnosis of type 2 diabetes mellitus for approximately 9 years, 87% had a prior myocardial infarction and 14% were current smokers. Hypertension (83%) and renal impairment (27% with an eGFR ≤60 mL/min/1.73 m^2) were prevalent co-morbid conditions. Use of medications to treat diabetes mellitus (e.g., metformin 73%, sulfonylurea 54%, insulin 41%), and ASCVD (e.g., statin 94%, aspirin 93%, renin-angiotensin system blocker 88%, beta-blocker 87%) was similar between patients randomized to NESINA and placebo at baseline. During the trial, medications to treat diabetes mellitus and ASCVD could be adjusted to ensure care for these conditions adhered to standard of care recommendations set by local practice guidelines.

The primary endpoint in EXAMINE was the time to first occurrence of a MACE defined as the composite of cardiovascular death, nonfatal myocardial infarction (MI), or nonfatal stroke. The trial was designed to exclude a pre-specified risk margin of 1.3 for the hazard ratio of MACE. The median exposure to trial drug was 526 days and 95% of the patients were followed to trial completion or death.

Table 12 shows the trial results for the primary MACE composite endpoint and the contribution of each component to the primary MACE endpoint. The upper bound of the confidence interval was 1.16 and excluded a risk margin larger than 1.3.

Table 12. Patients with MACE and Type 2 Diabetes Mellitus in EXAMINE
Composite of first event of CV death, nonfatal MI or nonfatal stroke (MACE) | NESINA |  | Placebo |  | Hazard Ratio
Composite of first event of CV death, nonfatal MI or nonfatal stroke (MACE) | Number of Patients (%) | Rate per 100 PY [Patient Years (PY)] | Number of Patients (%) | Rate per 100 PY | (98% CI)
Composite of first event of CV death, nonfatal MI or nonfatal stroke (MACE) | N=2701 |  | N=2679
Composite of first event of CV death, nonfatal MI or nonfatal stroke (MACE) | 305 (11.3) | 7.6 | 316 (11.8) | 7.9 | 0.96 (0.80, 1.16)
CV Death | 89 (3.3) | 2.2 | 111 (4.1) | 2.8
Non-fatal MI | 187 (6.9) | 4.6 | 173 (6.5) | 4.3
Non-fatal stroke | 29 (1.1) | 0.7 | 32 (1.2) | 0.8

The Kaplan-Meier based cumulative event probability is presented in Figure 4 for the time to first occurrence of the primary MACE composite endpoint by treatment arm. The curves for placebo and NESINA overlap throughout the duration of the trial. The observed incidence of MACE was highest within the first 60 days after randomization in both treatment arms (14.8 MACE per 100 PY), decreased from day 60 to the end of the first year (8.4 per 100 PY) and was lowest after one year of follow-up (5.2 per 100 PY).

Figure 4. Observed Cumulative Rate of MACE in EXAMINE

The rate of all cause death was similar between treatment arms with 153 (3.6 per 100 PY) recorded among patients randomized to NESINA and 173 (4.1 per 100 PY) among patients randomized to placebo. A total of 112 deaths (2.9 per 100 PY) among patients on NESINA and 130 among patients on placebo (3.5 per 100 PY) were adjudicated as cardiovascular deaths.

16 HOW SUPPLIED/STORAGE AND HANDLING

NESINA tablets are available as film-coated tablets containing 25 mg, 12.5 mg or 6.25 mg of alogliptin as follows:

25 mg tablet: light red, oval, biconvex, film-coated, with "TAK ALG-25" printed on one side, available in:

NDC 64764-250-30 | Bottles of 30 tablets
NDC 64764-250-90 | Bottles of 90 tablets
NDC 64764-250-50 | Bottles of 500 tablets

12.5 mg tablet: yellow, oval, biconvex, film-coated, with "TAK ALG-12.5" printed on one side, available in:

NDC 64764-125-30 | Bottles of 30 tablets
NDC 64764-125-90 | Bottles of 90 tablets
NDC 64764-125-50 | Bottles of 500 tablets

6.25 mg tablet: light pink, oval, biconvex, film-coated, with "TAK ALG-6.25" printed on one side, available in:

NDC 64764-625-30 | Bottles of 30 tablets
NDC 64764-625-90 | Bottles of 90 tablets

STORAGE AND HANDLING

Store at 25°C (77°F); excursions permitted to 15° to 30°C (59° to 86°F) [see USP Controlled Room Temperature].

17 PATIENT COUNSELING INFORMATION

Advise the patient to read the FDA-approved patient labeling (Medication Guide).

Pancreatitis

Inform patients that acute pancreatitis has been reported during use of NESINA. Educate patients that persistent, severe abdominal pain, sometimes radiating to the back, which may or may not be accompanied by vomiting, is the hallmark symptom of acute pancreatitis. Instruct patients to promptly discontinue NESINA and contact their physician if persistent severe abdominal pain occurs [see Warnings and Precautions (5.1)].

Heart Failure

Inform patients of the signs and symptoms of heart failure. Before initiating NESINA, patients should be asked about a history of heart failure or other risk factors for heart failure including moderate to severe renal impairment. Instruct patients to contact their healthcare providers as soon as possible if they experience symptoms of heart failure, including increasing shortness of breath, rapid increase in weight, or swelling of the feet [see Warnings and Precautions (5.2)].

Hypersensitivity Reactions

Inform patients that allergic reactions have been reported during use of NESINA. Instruct patients if symptoms of allergic reactions (including skin rash, hives and swelling of the face, lips, tongue and throat that may cause difficulty in breathing or swallowing) occur, patients should discontinue NESINA and seek medical advice promptly [see Warnings and Precautions (5.3)].

Hepatic Effects

Inform patients that postmarketing reports of liver injury, sometimes fatal, have been reported during use of NESINA. Instruct patients if signs or symptoms of liver injury occur, patients should discontinue NESINA and seek medical advice promptly [see Warnings and Precautions (5.4)].

Hypoglycemia with Concomitant Use with Insulin or Insulin Secretagogues

Inform patients that hypoglycemia can occur, particularly when an insulin secretagogue or insulin is used in combination with NESINA. Educate patients about the risks, symptoms and appropriate management of hypoglycemia [see Warnings and Precautions (5.5)].

Severe and Disabling Arthralgia

Inform patients that severe and disabling joint pain may occur with this class of drugs. The time to onset of symptoms can range from one day to years. Instruct patients to seek medical advice if severe joint pain occurs [see Warnings and Precautions (5.6)].

Bullous Pemphigoid

Inform patients that bullous pemphigoid may occur with this class of drugs. Instruct patients to seek medical advice if blisters or erosions occur [see Warnings and Precautions (5.7)].

Dosage

Instruct patients to take NESINA only as prescribed. Instruct patients if a dose is missed, not to double their next dose.

NES011 R12

MEDICATION GUIDE
NESINA® [nes-see′-na]
(alogliptin)
tablets

Read this Medication Guide carefully before you start taking NESINA and each time you get a refill. There may be new information. This information does not take the place of talking with your doctor about your medical condition or treatment. If you have any questions about NESINA, ask your doctor or pharmacist.

What is the most important information I should know about NESINA?
Serious side effects can happen to people taking NESINA, including:

1. Inflammation of the pancreas (pancreatitis): NESINA may cause pancreatitis which may be severe.
  Certain medical conditions make you more likely to get pancreatitis.
  Before you start taking NESINA:
  Tell your doctor if you have ever had:

- pancreatitis
- high blood triglyceride levels

- kidney problems
- stones in your gallbladder (gall stones)

- liver problems
- a history of alcoholism

Stop taking NESINA and call your doctor right away if you have pain in your stomach area (abdomen) that is severe and will not go away. The pain may be felt going from your abdomen through to your back. The pain may happen with or without vomiting. These may be symptoms of pancreatitis.

2. Heart failure: Heart failure means your heart does not pump blood well enough.
  Before you start taking NESINA:
  Tell your doctor if you have ever had heart failure or have problems with your kidneys.
  Contact your doctor right away if you have any of the following symptoms:

- increasing shortness of breath or trouble breathing especially when lying down

- an unusually fast increase in weight

- swelling of feet, ankles, or legs
- unusual tiredness

These may be symptoms of heart failure.

What is NESINA?

- NESINA is a prescription medicine used along with diet and exercise to improve blood sugar (glucose) control in adults with type 2 diabetes mellitus.
- NESINA is not for people with type 1 diabetes mellitus.

It is not known if NESINA is safe and effective in children under the age of 18.

Who should not take NESINA?
Do not take NESINA if you:

- Are allergic to any ingredients in NESINA or have had a serious allergic (hypersensitivity) reaction to NESINA. See the end of this Medication Guide for a complete list of the ingredients in NESINA.
  Symptoms of a serious allergic reaction to NESINA may include:

- swelling of your face, lips, throat and other areas on your skin
- raised, red areas on your skin (hives)

- difficulty with swallowing or breathing
- skin rash, itching, flaking or peeling

If you have any of these symptoms, stop taking NESINA and contact your doctor or go to the nearest hospital emergency room right away.

What should I tell my doctor before and during treatment with NESINA?
Before you take NESINA, tell your doctor if you:

- have heart failure
- have or have had inflammation of your pancreas (pancreatitis)
- have kidney or liver problems
- have other medical conditions
- are pregnant or plan to become pregnant. It is not known if NESINA can harm your unborn baby. Talk with your doctor about the best way to control your blood sugar while you are pregnant or if you plan to become pregnant
- are breastfeeding or plan to breastfeed. It is not known if NESINA passes into your breast milk. Talk with your doctor about the best way to feed your baby if you are taking NESINA

Tell your doctor about all the medicines you take, including prescription and over-the-counter medicines, vitamins and herbal supplements.
Know the medicines you take. Keep a list of them and show it to your doctor and pharmacist before you start any new medicine.
NESINA may affect the way other medicines work, and other medicines may affect how NESINA works. Contact your doctor before you start or stop other types of medicines.

How should I take NESINA?

- Take NESINA exactly as your doctor tells you to take it.
- Take NESINA 1 time each day with or without food.
- Do not split tablets.
- If you miss a dose, take it as soon as you remember. If you do not remember until it is time for your next dose, skip the missed dose, and take the next dose at your regular time. Do not take 2 doses of NESINA at the same time.
- If you take too much NESINA, call your doctor or your Poison Help Line right away at 1-800-222-1222.
- If your body is under stress, such as from fever, infection, accident or surgery, the dose of your diabetes mellitus medicines may need to be changed. Call your doctor right away.
- Stay on your diet and exercise programs and check your blood sugar as your doctor tells you to.
- Your doctor may do certain blood tests before you start NESINA and during treatment as needed. Your doctor may change your dose of NESINA based on the results of your blood tests due to how well your kidneys are working.
- Your doctor will check your diabetes mellitus with regular blood tests, including your blood sugar levels and your hemoglobin A1C.

What are the possible side effects of NESINA?
NESINA can cause serious side effects, including:
See "What is the most important information I should know about NESINA?"

- Serious allergic (hypersensitivity) reactions such as:

- swelling of your face, lips, throat and other areas on your skin
- raised, red areas on your skin (hives)

- difficulty swallowing or breathing
- skin rash, itching, flaking or peeling

If you have these symptoms, stop taking NESINA and contact your doctor right away or go the nearest hospital emergency room.

- Liver problems. Call your doctor right away or go to the nearest hospital emergency room if you have unexplained symptoms, such as:

- nausea or vomiting
- loss of appetite

- stomach pain
- dark urine

- unusual or unexplained tiredness
- yellowing of your skin or the whites of your eyes

- Low blood sugar (hypoglycemia). If you take NESINA with another medicine that can cause low blood sugar, such as a sulfonylurea or insulin, your risk of getting low blood sugar is higher. The dose of your sulfonylurea medicine or insulin may need to be lowered while you take NESINA. If you have symptoms of low blood sugar, you should check your blood sugar and treat if low, then call your doctor. Signs and symptoms of low blood sugar include:

- shaking or feeling jittery
- fast heartbeat

- sweating
- change in vision

- hunger
- confusion

- headache
- dizziness

- change in mood

- Joint pain. Some people who take medicines called DPP-4 inhibitors like NESINA, may develop joint pain that can be severe. Call your doctor if you have severe joint pain.
- Skin reaction. Some people who take medicines called DPP-4 inhibitors, like NESINA, may develop a skin reaction called bullous pemphigoid that can require treatment in a hospital. Tell your doctor right away if you develop blisters or the breakdown of the outer layer of your skin (erosion). Your doctor may tell you to stop taking NESINA.

The most common side effects of NESINA include stuffy or runny nose and sore throat, headache, or cold-like symptoms (upper respiratory tract infection).
Tell your doctor if you have any side effect that bothers you or that does not go away.
These are not all the possible side effects of NESINA. For more information, ask your doctor or pharmacist.
Call your doctor for medical advice about side effects. You may report side effects to FDA at 1-800-FDA-1088.

How should I store NESINA?
Store NESINA at room temperature between 68°F to 77°F (20°C to 25°C).
Keep NESINA and all medicines out of the reach of children.

General information about the safe and effective use of NESINA.
Medicines are sometimes prescribed for purposes other than those listed in the Medication Guide. Do not take NESINA for a condition for which it was not prescribed. Do not give NESINA to other people, even if they have the same symptoms you have. It may harm them.
This Medication Guide summarizes the most important information about NESINA. If you would like to know more information, talk with your doctor. You can ask your doctor or pharmacist for information about NESINA that is written for health professionals.
For more information go to www.NESINA.com or call 1-877-TAKEDA-7 (1-877-825-3327).

What are the ingredients in NESINA?
Active ingredient: alogliptin
Inactive ingredients: croscarmellose sodium, hydroxypropyl cellulose, magnesium stearate, mannitol, and microcrystalline cellulose. In addition, the film coating contains the following inactive ingredients: ferric oxide (red or yellow), hypromellose, polyethylene glycol, and titanium dioxide and is marked with printing ink (Gray F1).
Distributed by: Takeda Pharmaceuticals America, Inc., Cambridge, MA 02142.
NESINA is a registered trademark of Takeda Pharmaceutical Company Limited.
©2025 Takeda Pharmaceuticals America, Inc. All rights reserved.

This Medication Guide has been approved by the U.S. Food and Drug Administration.

NES011 R12

February 2025

PRINCIPAL DISPLAY PANEL - 6.25 mg Tablet Bottle Label

NDC 64764-625-30

Nesina®
(alogliptin) tablets

6.25 mg

Dispense with
Medication Guide

30 Tablets

Takeda

Rx Only

PRINCIPAL DISPLAY PANEL - 12.5 mg Tablet Bottle Label

NDC 64764-125-30

Nesina®
(alogliptin) tablets

12.5 mg

Dispense with
Medication Guide

30 Tablets

Takeda

Rx Only

PRINCIPAL DISPLAY PANEL - 25 mg Tablet Bottle Label

NDC 64764-250-30

Nesina®
(alogliptin) tablets

25 mg

Dispense with
Medication Guide

30 Tablets

Takeda

Rx Only